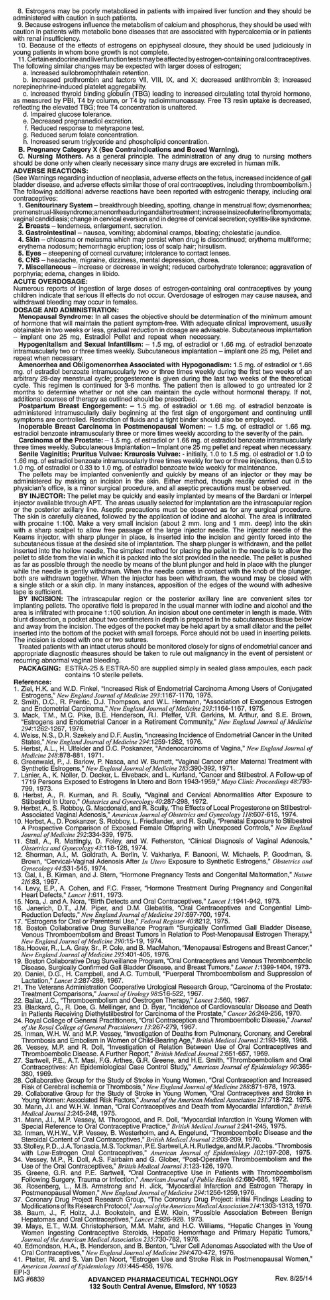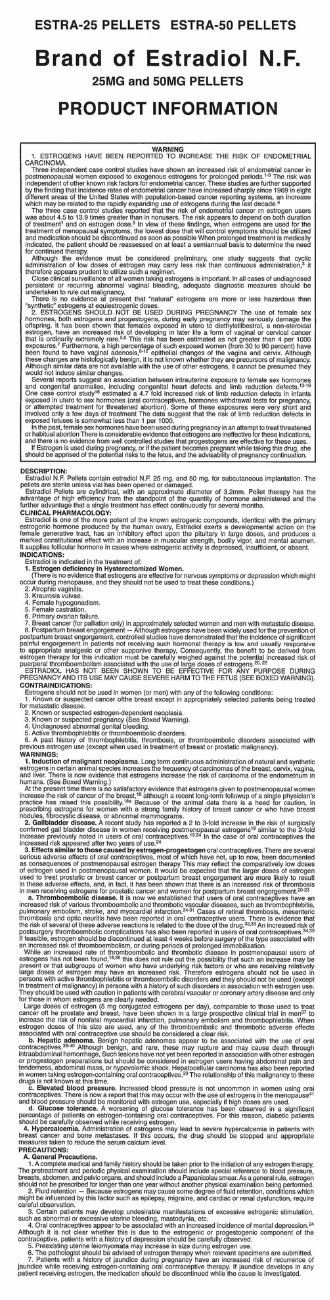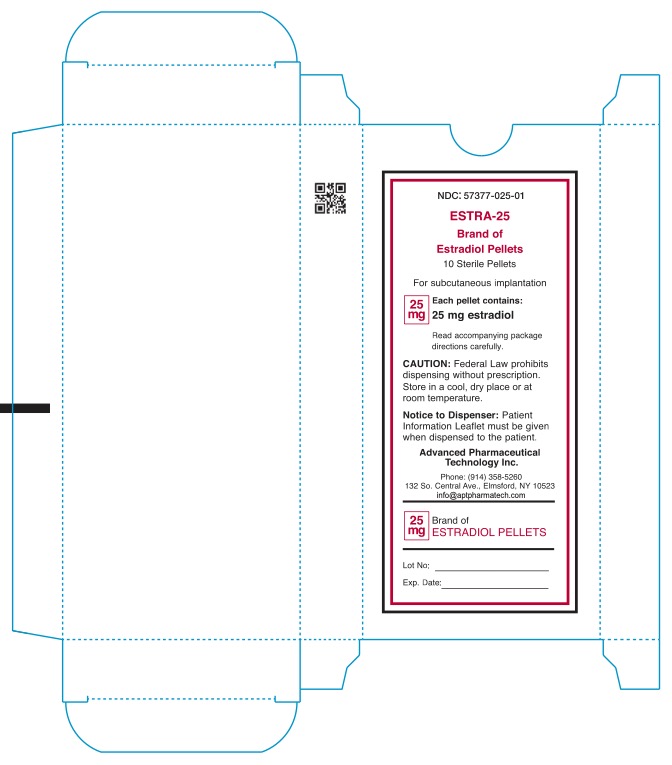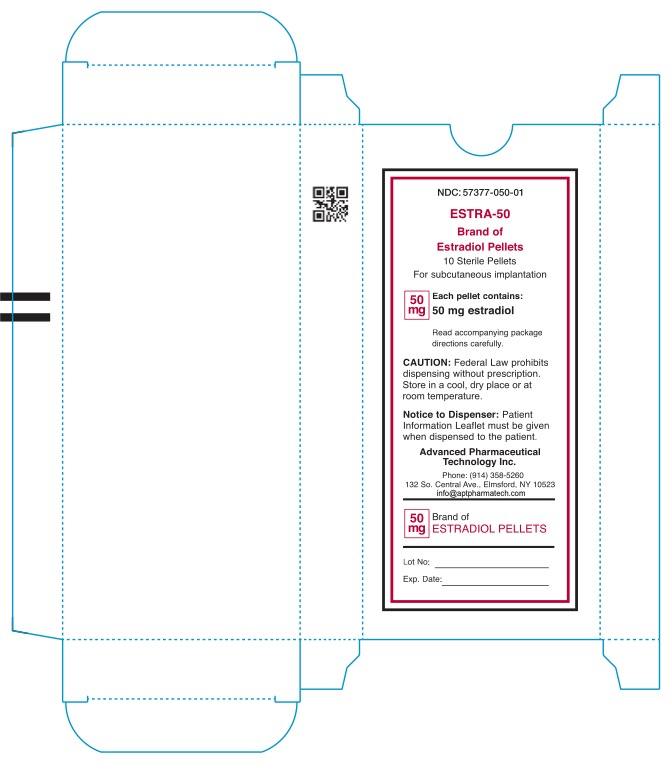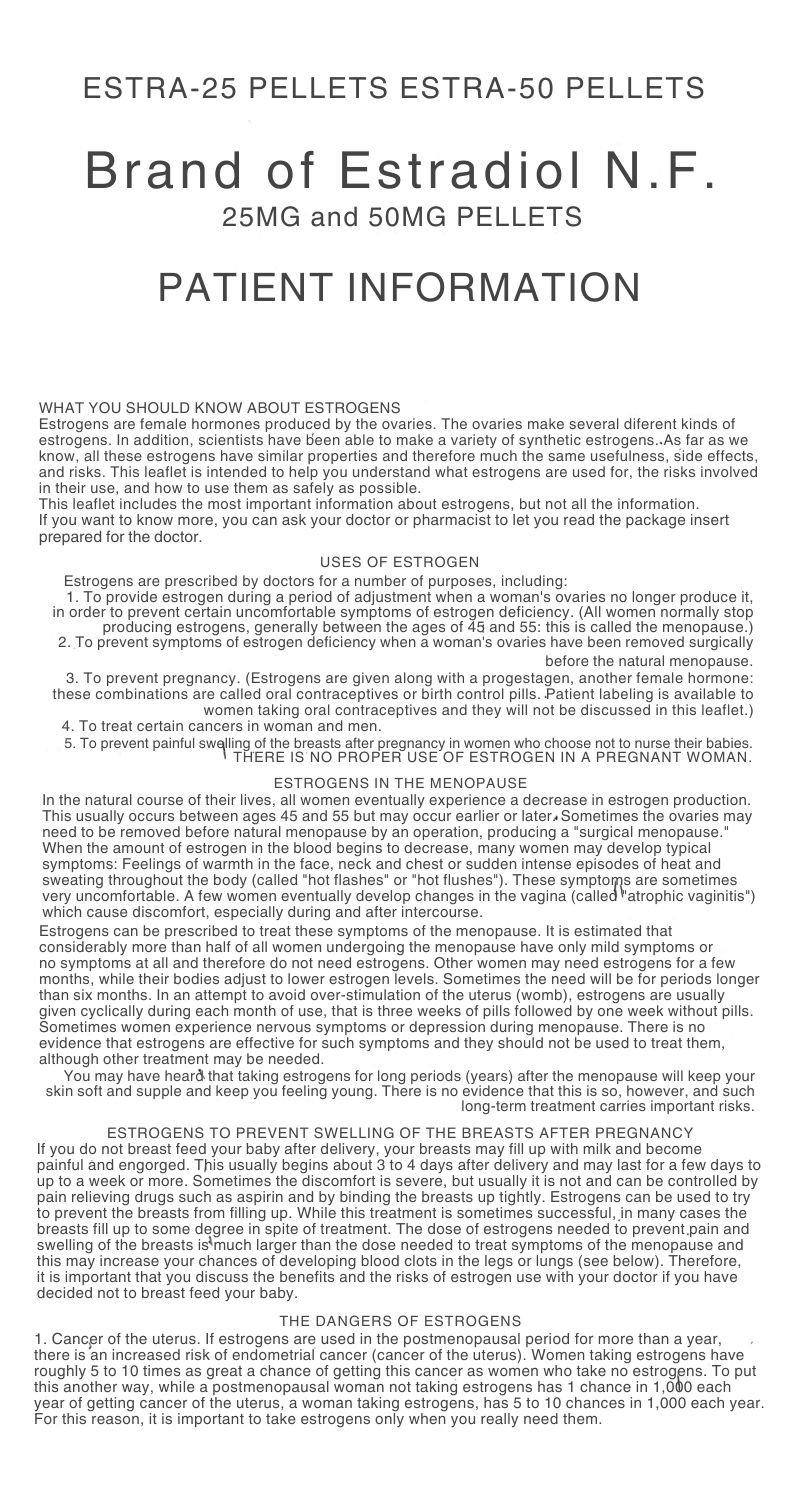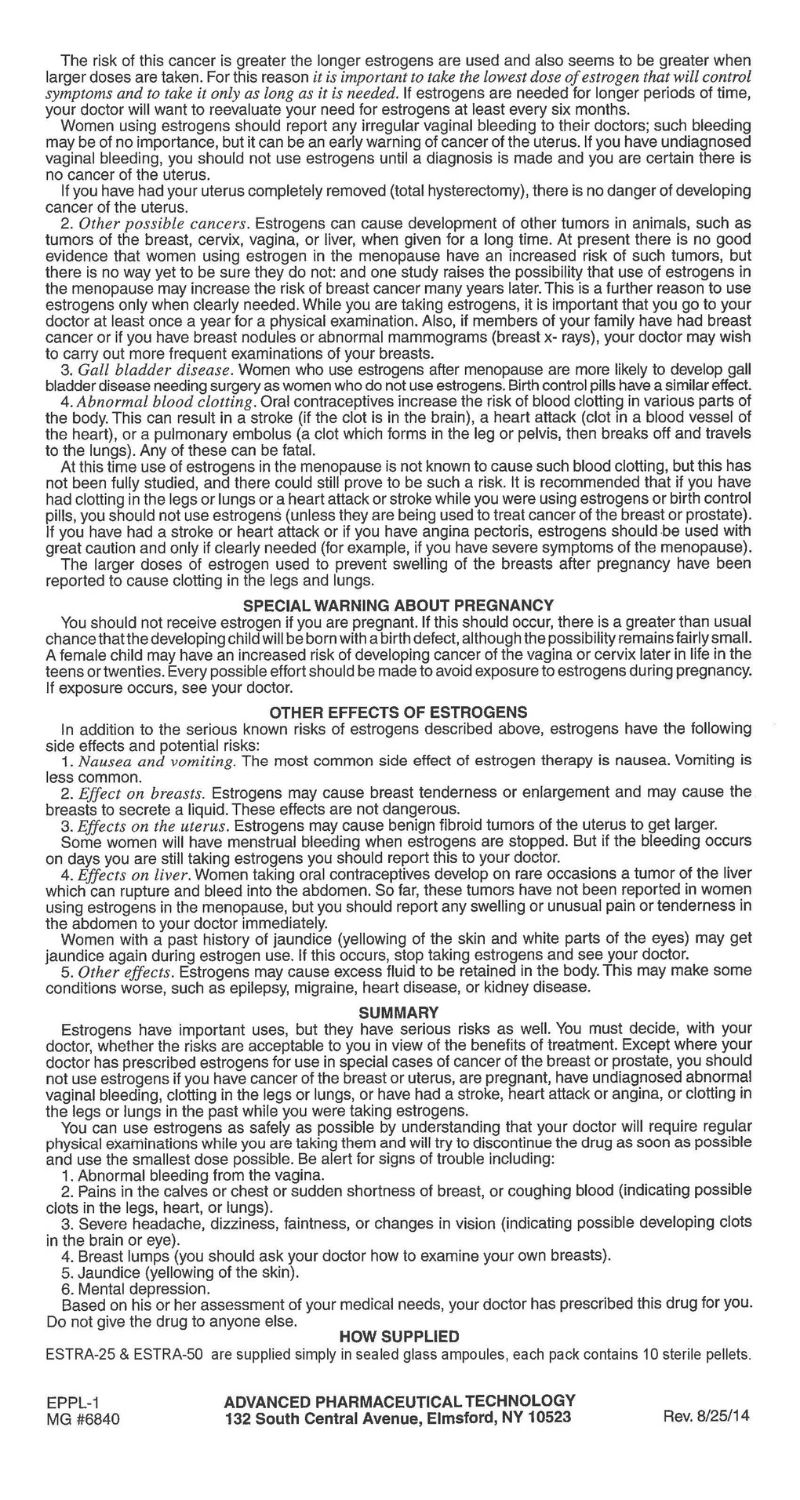 DRUG LABEL: Estra-50
NDC: 57377-050 | Form: PELLET, IMPLANTABLE
Manufacturer: Advanced Pharmaceutical Technology, Inc.
Category: prescription | Type: HUMAN PRESCRIPTION DRUG LABEL
Date: 20240927

ACTIVE INGREDIENTS: ESTRADIOL 50 mg/1 1
INACTIVE INGREDIENTS: STEARIC ACID; POVIDONE

Estra-50 & Estra-25

Warning

1. ESTROGENS HAVE BEEN REPORTED TO INCREASE THE RISK OF ENDOMETRIAL CARCINOMA.

Three independent case control studies have shown an increased risk of endometrial cancer in postmenopausal women exposed to exogenous estrogens for prolonged periods.^1-3The risk was independent of other known risk factors for endometrial cancer. These studies are further supported by the finding that incidence rates of endometrial cancer have increased sharply since 1969 in eight different areas of the United States with population-based cancer reporting systems, an increase which may be related to rapidly expanding use of estrogens during the last decade.^4

The three case control studies reported that the risk of endometrial cancer in estrogen users was about 4.5 to 13.9 times greater than in nonusers. The risk appears to depend on both duration of treatment^1and on estrogen dose.^3In view of these findings, when estrogens are used for the treatment of menopausal symptoms, the lowest dose that will control symptoms should be utilized and medication should be discontinued as soon as possible. When prolonged treatment is medically indicated, the patient should be reassessed on at least a semiannual basis to determine the need for continued therapy.

Although the evidence must be considered preliminary, one study suggests that cyclic administration in low doses of estrogen may carry less risk than continuous administration,^3it therefore appears prudent to utilize such a regimen.

Close clinical surveillance of all women taking estrogens is important. In all cases of undiagnosed persistant or recurring abnormal vaginal bleeding, adequate diagnostic measures should be undertaken to rule out malignancy.

There is no evidence at present that "natural" estrogens are more or less hazardous than "synthetic" estrogens at equiestrogenic doses.

2. ESTROGENS SHOULD NOT BE USED DURING PREGNANCY The use of female sex hormones, both estrogens and progestogens, during early pregnancy may seriously damage the offspring. It has been shown that females exposed in utero to diethylstilbestrol, a non-steroidal estrogen, have increased risk of developing in later life a form of vaginal or cervical cancer that is ordinarily extremely rare.^5,6This risk has been estimated as not greater than 4 per 1000 exposures.^7Furthermore, a high percentage of such exposed women (from 30 to 90 percent) have been found to have vaginal adenosis,^8-12epithelial changes of the vagina and cervix. Although these changes are histologically benign, it is not known whether they are precursors of malignancy. Although similar data are not available with the use of other estrogens, it cannot be presumed they would not induce similar changes.

Several reports suggest an association between intrauterine exposure to female sex hormones and congenital anomalies, including congenital heart defects and limb reduction defects.^13-16One case control study^16estimated a 4.7 fold increased risk of limb reduction defects in infants exposed in utero to sex hormones (oral contraceptives, hormones withdrawl tests for pregnancy, or attempted treatment for threatened abortion). Some of these exposures were very short and involved only a few days of treatment. The data suggest that the risk of limb reduction defects in exposed fetuses is somewhat less than 1 per 1000.

In the past, female sex hormones have been used during pregnancy in an attempt to treat threatened or habitual abortion. There is no considerable evidence from well controlled studies that progestogens are effective for these uses.

If Estrogen is used during pregnancy, or if the patient becomes pregnant while taking this drug, she should be apprised of the potential risks to the fetus, and the advisability of pregnancy continuation.

DESCRIPTION:

Estradiol N.F. Pellets contain N.F. 25mg and 50mg for subcutaneous implantation. The pellets are sterile unless vial has been opened or damaged.

Estradiol Pellets are cylindrical, with an approximate diameter of 3.2mm. Pellet therapy has the advantage of high efficiency from the standpoint of the quality of the hormone administered and the further advantage that a single treatment has effect continuously for several months.

CLINICAL PHARMACOLOGY:

Estradiol is one of the more potent of the known estrogenic compounds, identical with the primary estrogenic hormone produced by the human ovary. Estradiol exerts a developmental action on the female generative tract, has an inhibitory effect upon the pituitary in large doses, and produces a marked constitutional effect with an increase in muscular strength, body vigor, and mental acumen. It supplies follicular hormone in cases where estrogenic activity is depressed, insufficient, or absent.

INDICATIONS:

Estradiol is indicated in the treatment of:

1. Estrogen deficiency in Hysterectomized Women.

(There is no evidence that estrogens are effective for nervous symptoms or depression which might occur during menopause, and they should not be used to treat these conditions.)

2. Atrophic vaginitis.

3. Kraurosis vulvae.

4. Female hypogonadism.

5. Female castration.

6. Primary ovarian failure.

7. Breast cancer (for palliation only) in approximately selected women and men with metastatic disease.

8. Postpartum breast engorgement - Although estrogens have been widely used for the prevention of postpatum breast engorgement, controlled studies have demonstrated that the incidence of significant painful engorgement in patients not receiving such hormonal therapy is low and usually responsive to appropriate analgesic or other supportive therapy. Consequently, the benefit to be derived from estrogen therapy for this indication must be carefully weighed against the potential increased risk or puerperal thromboembolism associated with the use of large doses of estrogen.^20,22

ESTRADIOL HAS NOT BEEN SHOWN TO BE EFFECTIVE FOR ANY PURPOSE DURING PREGNANCY AND ITS USE MAY CAUSE SEVERE HARM TO THE FETUS (SEE BOXED WARNING).

CONTRAINDICATIONS:

Estrogens should not be used in women (or men) with any of the following conditions:

1. Known or suspected cancer of the breast except in appropriately selected patients being treated for metastatic disease.

2. Known or suspected estrogen-dependant neoplasia.

3. Known or suspected pregnancy (See Boxed Warning).

4. Undiagnosed abnormal genital bleeding.

5. Active thrombophlebitis or thromboembolic disorders.

6. A past history of thrombophlebitis, thrombosis, or thromboembolic disorders associated with previous estrogen use (except when used in treatment of breast prostatic malignancy).

WARNINGS:

1. Induction of malignant neoplasma. Long term continuous administration of natural and synthetic estrogen in certain animal species increases the frequency of carcinomas of the breast, cervix, vagina, and liver. There is new evidence that estrogens increase the risk of carcinoma of the endometrium in humans. (See Boxed Warning.)

At the present time there is no satisfactory evidence that estrogens given to postmenopausal women increase the risk of cancer of the breast,^18although a recent long-term followup of a single physician's practice has raised this possibility.18aBecause of the animal data there is a heed for caution, in prescribing estrogens for women with a strong history of breast cancer or who have breast nodules, fibrocystic disease, or abnormal mammograms.

2. Gallbladder disease. A recent study has reported a 2 to 3-fold increase in the risk of surgically confirmed gall bladder disease in women receiving postmenopausal estrogens^18similar to the 2 fold increase previously noted in users of oral contraceptives.^19,24In the case of oral contraceptives the increased risk appeared after two years of use.^24

3. Effects similar to those caused by estrogen-progestogen oral contraceptives. There are several serios adverse effects or oral contraceptives, most of which have not, up to now, been documented as consequences of postmenopausal estrogen therapy. This may reflect the comparatively low doses of estrogen used in postmenopausal women. It would be expected that the larger doses of estrogen used to treat prostatic or breast cancer or postpartum breast engorgement are more likely to result in these adverse effects, and, in fact,it has been shown that there is an increased risk of thrombosis in men receiving estrogens for prostatic cancer and women for postpartum breast engorgement.

a. Thromboembolic disease. It is now we establish that users of oral contraceptives have an increased risk of various thromboembolic and thrombotic vascular disease, such as thrombophlebitis, pulminary embolism, stroke, and myocardial infarction.^24-31Cases of retinal thrombosis, mesenteric thrombosis and optic neuritis have been reported in oral contraceptive users. There is evidence that the risk of several of these adverse reactions is related to the dose of the drug.^32,33An increase risk of post surgery thromboembolic complications has also been reported in users of oral contrceptives.^34,35if feasable, estrogen should be discontinued at least 4 weeks before surgery of the type associated with an increased risk of thromboembolism, or during periods of prolonged immobilization.

While an increased rate of thromboembolic and thrombotic disease in postmenopausal users of estrogen has not been found,^18,36this does not rule out that such an increase may be present or that subgroups of women having underlying risk factors or who are receiving relatively large doses of estrogen may have an increased risk. Therefore estrogens should not be used in persons with active thrombophlebitis or thromboembolic disorders and they should not be used (except in treatent of malignancy) in persons with a history of such disorders in association with estrogen use. They should be used with caution in patients with cerebral vascular or coronary artery disease and only for those in whom estrogens are clearly needed.

Large doses of estrogens (5mg conjugated estrogens per day), comparable to those used to treat cancer of the prostate and breast, have been shown in a large prospective clinical trial in men^37to increase the risk of nonfatal myocardial infarction, pulmonary embolism, and thrombophlebitis. When estrogen doses of this size are used, any of the thromboembolicand thrombotic adverse effects associated with oral contraceptive use should be considered a clear risk.

b. Hepatic adenoma. Benign hepatic adenomas appear to be associated with the use of oral contraceptives.^38-40Although benign, and rare, these may rupture and may cause death through intraabdominal hemorrhage. Such lesions have not yet been reported in association with other estrogen or progestogen preparations but should be considered in estrogen users having abdominal pain and tenderness, abdominal mass, or hypovolemic shock. Hepatocellular carcinoma has also been reported in women taking estrogen-containing oral contraceptives.^39The relationship of this malignancy to these drugs is not know at this time.

c. Elevated blood pressure. Increased blood pressure is not uncommon in women using oral contraceptives. There is now a report that this may occur with the use of estrogens in menopause^41and blood pressure should be monitored with estrogen use, especially if high doses are used.

d. Glucose tolerance. A worsening of glucose tolerance has been observed in a significant percentage of patients on estrogen-containing oral contraceptives. For this reason, diabetic patients should be carefully observed while receiving estrogen.

4. Hypercalcemia. Administration of estrogens may lead to severe hypercalceemia in patients with breast cancer and bone metastases. If this occurs, the drug should be stopped and appropriate measures taken to reduce the serum calcium level.

PRECAUTIONS:

A. General Precautions.

1. A complete medical and family history should be taken prior to initiation of any estrogen therapy. The pretreatment and periodic physical examination should include special reference to blood pressure, breasts, abdomen, and pelvic organs, and should include a Papnicolau smear. As a general rule, estrogen should not be prescribed for longer than one year without a physical examination being performed.

2. Fluid retention - Because estrogens may cause some degree of fluid retention, conditions which may be influenced by this factor such as epilepsy, migraine, and cardiac or renal dysfunction, require careful observation.

3. Certain patients may develope undesirable manifestations of excessive estrogenic stimulation, such as abnormal or excessive uterine bleeding, mastodynia, etc.

4.Oral contraceptives appear to be associated with an increased incidence of mental depression.^24Although it is not clear whether this is due to the estrogenic or progestogenic component of the contraceptive, patients with a history of depression should be carefully observed.

5. Preexisting uterine leiomyomata may increase in size during estrogen use.

6. The pathologist should be advised of estrogen therapy when relevent specimens are submitted.

7. Patients with a history of jaundice during pregnancy have an increased risk of reccurance of jaundice while receiving estrogen-containing oral contraceptive therapy. If jaundice develops in any patient receiving estrogen, the medication should be discontinued while the cause is investigated.

8. Estrogens may be poorly metabolized in patients with impaired liver function and they should be administered with caution in such patients.

9. Because estrogens influence the metabolism of calcium and phosphorous, they should be used with caution in patients with metabolic bone diseases that are associated with hypercalcemia or in patients with renal insufficiency.

10. Because of the effects of estrogens on epiphyseal closure, they should be used judiciously in young patients in whom bone growth is not complete.

11. Certain endocrine and liver function tests may be affected by estrogen-containing oral contraceptives. The following similar changes may be expected with larger doses of estrogen;

a. Increased sullobromophthalein retention.

b. Increased prothrombin and factors VII, VIII, IX, and X; decreased antithrombin 3; increased norepinephrine-induced platelet aggregability.

c. Increased thyroid binding globulin (TGB) leading to increased circulating total thyroid hormone, as measured by PBI, T4 by column, or T4 by radioimmunoassay. Free T3 resin uptake is decreased, reflecting elevated TBG; free T4 concentration is unaltered.

d. Impaired glucose toerance.

e. Decreased pregnanediol excretion.

f. Reduced response to metyrapone test.

g. Reduced serum folate concentration.

h. Increased serum triglyceride and phospholipid concentration.

B. Pregnancy Category X (See Contraindications and Boxed Warning).

C. Nursing Mothers. As a general principal, the administration of any drug to nursing mothers should be done only when clearly necessary since many drugs are excreted in human milk.

ADVERSE REACTIONS:

(See Warnings regarding induction of neoplasia, adverse effects on the fetus, increased incidence of gall bladder disease, and adverse effects similar to those of oral contraceptives, including thromboembolism.) The following additional adverse reactions have been reported with estrogenic therapy, including oral cantraceptives:

1. Genitourinary System - breakthrough bleeding, spotting, change in menstrual flow; dysmenorrhea; premenstrual-like syndrome; amenorrhea during and after treatment; increase in size of uterine fibromyomata; vaginal candidas; change in cervical eversion and in degree of cervical secretion; cystitis-like syndrome.

2. Breasts - tenderness, enlargement, secretion

3. Gastrointestinal - nausea, vomiting,; abdominal cramps, bloating; cholestatic jaundice.

4. Skin - chloasma or melasma which may persist when drug is discontinued; erythema multiforme; erythema nodosum; hemorrhagic eruption; loss of scalp hair; hirsutism.

5. Eyes - steepening of corneal curvature; intolerance to contact lenses.

6. CNS - headache, migraine, dizziness, mental depression, chorea.

7. Miscellaneous - increase or decrease in weight;reduced carbohydrate tolerance; aggrevation of porphyria; edema, changes in libido.

ACUTE OVERDOSAGE:

Numerous reports of ingestion of large doses of estrogen-containing oral contraceptives by young children indicate that serious ill effects do not occur. Overdosage of estrogen may cause nausea, and withdrawl bleeding may occur in females.

DOSAGE AND ADMINISTRATION:

Menopausal Syndrome: In all cases the objective should be determination of the minimum amount of hormone that will maintain the patient symptom-free. With adequate clinical improvement, usually obtainable in two weeks or less, gradual reduction in dosage are advisable. Subcutaneous implantation- implant one 25mg, Estradiol Pellet and repeat when necessary. The pellets provide constant estrogen levels for approximately 3 months.

Hypogenitalism and Sexual Infantilism: - 1.5mg of estradiol or 1.66mg of estradiol benzoate intramuscularly two to three times weekly. Subcutaneous implantation - implant one 25mg, Pellet and repeat when necessary.

Amenorrhea and Oligomenorrhea Associated with Hypogonadism: 1.5mg of estradiol or 1.66mg of estradiol benzoate intramuscularly two to three times weekly during the first two weeks of an arbitrary 28-day menstrual cycle; progesterone is given the last two weeks of the theoretical cycle. This regimen is continued for 3-6 months. The patient then is allowed to go untreated for 2 months to determine whether or not she can maintain the cycle without hormonal therapy. If not, additional courses of therapy as outlined should be prescribed.

Postpartum Breast Engorgement: - 1.5mg of estradiol or 1.66mg of estradiol benzoate is administered intramuscularly daily begining at the first sign of engorgement and continuing until the symptoms are controlled. Restriction of fluids and a tight binder should also be employed.

Inoperable Breast Carcinoma in Postmenopausal Women: - 1.5mg of estradiol or 1.66mg of estradiol benzoate intramuscularly three or more times weekly according to the severity of the pain.

Carcinoma of the Prostate: - 1.5mg of estradiol or 1.66mg of estradiol benzoate intramuscularly three times weekly. Subcutaneous Implantation - Implant one 25mg pellet and repeat when necessary.

Senile Vaginitis; Pruritis Vulvae; Kraurosis Vulvae: - 1.0 to 1.5mg of estradiol or 1.0 to 1.66mg of estradiol benzoate intramuscularly three times weekly for two or three injections, then 0.5 to 1.0mg of estradiol or 0.33 to 1.0mg of estradiol benzoate twice weekly for maintainance.

The pellets may be implanted conveniently and quickly by means of an injector or they may be administered by making an incision in the skin. Either method, though readily carried out in the physician's office, is a minor surgical procedure, and all aseptic precautions must be observed.

BY INJECTOR: The pellet may be quickly and easily implanted by means of the Bardani or Bartor Pellet Injectors. The areas usually selected for implantation are the intrascapular region or the posterior axillary line. Aseptic precautions must be observed for any surgical procedure. The skin is carefully cleaned, followed by the application of iodine and alcohol. The area is infiltrated with procaine 1:100. Make a very small incision (about 2mm long and 1mm deep) into the skin with a sharp scalpel to allow free passage of the large injector needle. The injector needle of the Kearns injector, with sharp plunger in place, is inserted into the incision and gently forced into the subcutaneous tissue at the desired site of implantation. The sharp plunger is withdrawn, and the pellet inserted into the hollow needle. The simplest method for placing the pellet in the needle is to allow the pellet to slide from the vial in which it is packed into the slot provided in the needle. The pellet is pushed as far as possible through the needle by means of the blunt plunger and held in place with the plunger while the needle is gently withdrawn. When the needle comes in contact with the knob of the plunger, both are withdrawn together. When the injector has been withdrawn, the wound may be closed with a single stitch or a skin clip. In many instances, apposition of the edges of the wound with adhesive tape is sufficient.

BY INCISION: The intrascapular region or the posterior axillary line are convenient site for implanting pellets. The operative field is prepared in the usual manner with iodine and alcohol and the area is infiltrated with procaine 1:100 solution. An incision about 1 centimeter in length is made. With blunt dissection, a pocket about two centimeters in depth is prepared in the subcutaneous tissue below and away from the incision. The edges of the pocket may be held apart by a smal dilator and the pellet inserted into the bottom of the pocket with small forceps. Force should not be used when inserting pellets. The incision is closed with one or two sutures.

Treated patients with an intact uterus should be monitored closely for signs of endometrial cancer and appropriate diagnostic measures should be taken to rule out malignancy in the event of persistent or recurring abnormal vaginal bleeding.

PACKAGING:

ESTRA-25 & ESTRA-50 are supplied simply in sealed glass ampoules, each pack

contains 10 sterile pellets.

References:

1. Zeil, H.K. and W.D. Finkle, Increased Risk of Endometrial Carcinoma Among Users of Conjugated Estrogens, New England Journal of Medicine 293:1167-1170, 1975.

2. Smith, D.C., R. Prentic, D.J. Thompson, and W.L. Hermann, Association of Exogenous Estrogen and Endometrial Carcinoma, New England Journal of Medicine 293:1164-1167, 1975

3. Mack, T.M., M.C. Pike, B.E. Henderson, R.I. Pfeffer, V.R. Gerkins, M. Arthur, and S.E. Brown, Estrogens and Endometrial Cancer in a Retirement Community, New England Journal of Medicine 294:1262-1267, 1976.

4. Weiss, N.S., D.R. Szekely and D.F. Austin, Increasing Incidence of Endometrial Cancer in the United States, New England Journal of Medicine 294:1259-1262, 1976.

5. Herbst, A.L., H. Ulfelder and D.C. Poskanzer, Adenocarcinoma of Vagina, New England Journal of Medicine 248:878-881, 1971.

6. Greenwald, P., J. Barlow, P. Nasca, and W. Burnett, Vaginal Cancer after Maternal Treatment with Synthetic Estrogens, New England Journal of Medicine 285:390-392, 1971.

7. Lanier, A., K. Noller, D. Decker, L. Elveback, and L. Kurland, Cancer and Stilbestrol. A Follow-up of 1719 Persons Exposed to Estrogens In Utero and Born 1943-1959, Mayo Clinic Proceedings 48:793- 799, 1973.

8. Herbst, A., R. Kurman, and R. Scully, Vaginal and Cervical Abnormalities After Exposure to Stilbestrol ln Utero, Obstetrics and Gynecology 40:287-298, 1972.

9. Herbst, A., S. Robboy, G. Macdonald, and R. Scully, The Effects of Local Progesterone on Stilbestrol- Associated Vaginal Adenosis, American Journal of Obstetrics and Gynecology 118:607-615, 1974.

10. Herbst, A., D. Poskanzer, S. Robboy, L. Friedlander, and R. Scully, Prenatal Exposure to Stilbestrol A Prospective Comparison of Exposed Female Offspring with Unexposed Controls, New England Journal of Medicine 292:334-339, 1975.

11. Stall, A., R. Mattingly, D. Foley, and W. Fetherston, Clinical Diagnosis of Vaginal Adenosis, Obstetrics and Gynecology 43:118-128, 1974.

12. Sherman, A.l., M. Goldrath, A. Berlin, V. Vakhariya, F. Banooni, W. Michaels, P. Goodman, S. Brown, Cervical-Vaginal Adenosis After In Utero Exposure to Synthetic Estrogens, Obstetrics and Gynecology 44:531-545, 1974.

13. Gal, I., B. Kirman, and J. Stern, Hormone Pregnancy Tests and Congenital Maltormation, Nature 216:83, 1967.

14. Levy, E.P., A. Cohen, and F.C. Fraser, Hormone Treatment During Pregnancy and Congenital Heart Defects, Lancet 1:611, 1973. 15. Nora, J. and A. Nora, Birth Detects and Oral Contraceptives, Lancet 1:1941-942, 1973.

16. Janerich, D.T., J.M. Piper, and D.M. Glebatitis, Oral Centraoeptives and Congential Limb-Reduction Defects, New England Journal of Medicine 291:697-700, 1974.

17. Estrogens for Oral or Parenteral Use, Federal Register 40:8212, 1975.

18. Boston Collaborative Drug Surveillance Program Surgically Con rmed Gall Bladder Disease, Venous Thromboembolism and Breast Tumors in Relation to Post-Menopausal Estrogen Therapy, New England Journal of Medicine 290:15-19, 1974.

18a.Hoover, R., L.A. Gray, Sr., P. Cole, and B. MacMahon, Menopausal Estrogens and Breast Cancer, New England Journal of Medicine 295:401-405, 1976.

19. Boston Collaborative Drug Surveillance Program, Oral Contraceptives and Venous Thromboembclic Disease, Surgically Confirmed Gall Bladder Disease, and Breast Tumors, Lancet 1:1399-1404, 1973.

20. Daniel, D.G., H. Campbell, and A.C. Turnbull, Puerperal Thromboembolism and Suppression of Lactation, Lancet 2:287-289, 1967.

21. The Veterans Administration Cooperative Urological Research Group, Carcinoma of the Prostate: Treatment Comparisons, Journal of Urology 98:516-522, 1967.

22. Bailar, J.C., Thromboembolism and Oestrogen Therapy, Lancet 2:560, 1967.

23. Blackard, C., R. Doe, G. Mellinger, and D. Byar, Incidence of Cardiovascular Disease and Death in Patients Receiving Diethylstilbestrol for Carcinoma of the Prostate, Cancer 26:249-256, 1970.

24. Royal College of General Practitioners, Oral Contraception and Thromboembolic Disease, Journal of the Royal College of General Practitioners 13:267-279, 1967.

25. Inman, W.H. W. and M.P. Vessey, Investigation of Deaths from Pulmonary, Coronary, and Cerebral Thrombosis and Embolism in Women of Child-Bearing Age, British Medical Journal 2:193-199, 1968.

26. Vessey, M.P. and R. Doll, Investigation of Relation Between Use of Oral Contraceptlves and Thromboembolic Disease. A Further Report, British Medical Journal 2:651-657, 1969.

27. Sartweil, P.E., A.T. Masi, F.G. Arthes, G.R. Greene, and H.E. Smith, Thromboembolism and Oral Contraceptives: An Epidemiological Case Control Study, American Journal of Epidemiology 90:365- 380, 1969.

28. Collaborative Group for the Study of Stroke in Young Women, Oral Contraception and Increased Risk of Cerebral ischemia or Thrombosis, New England Journal of Medicine 288:871-878, 1973.

29. Collaborative Group for the Study of Stroke in Young Women, Oral Contraceptives and Stroke in Young Women: Associated Risk Factors, Journal of the American Medical Association 231:718-722. 1975.

30. Mann, J.l. and W.H.W. Inman, Oral Contraceptives and Death from Myocardial Infarction, British Medical Journal 2:245-248, 1975.

31. Mann, J.|., M.P. Vessey, M. Thorogood, and R. Doll, Myocardial lnfarction in Young Women with Special Reference to Oral Contraceptive Practice, British Medical Journal 2:241-245, 1975.

32. Inman, W,H.W., V.P. Vessey, B. Westerholm, and A. Engelund, Thromboembolic Disease and the Steroidal Content of Oral Contraceptives, British Medical Journal 2:203-209, 1970.

33.Stolley, P.D., J.A.Tonascia, M.S.Tockman, P.E.Sartwell, A.H.Rutledge, and M.P, Jacobs.Thrombosis with Low-Estrogen Oral Contraceptives, American Journal of Epidemiology 102:197-208, 1975.

34. Vessey, M.P., R. Doll, A.S. Fairbairn and G. Glober, Post-Operative Thromboembolism and the Use of the Oral Contraceptives, British Medical Journal 3:123-126, 1970.

35. Greene, G.R. and P.E. Sartwell, Oral Contraceptive Use in Patients with Thromboembolism Following Surgery, Trauma or lnfection, American Journal of Public Health 62:680-685, 1972.

36. Rosenberg, L., M.B. Armstrong and H. Jick, Myocardial Infarction and Estrogen Therapy in Postmenopausal Women, New England Journal of Medicine 294:1256-1259,1976.

37. Coronary Drug Project Research Group, The Coronary Drug Project: initial Findings Leading to Modi cations of Its Research Protocol, Journal of the American Medical Association 214:1303-1313, 1970.

38. Baum, J., F, Holtz, J.J. Bookstein, and E.W. Klein, Possible Association Between Benign Hepatomas and Oral Contraceptives, Lancet 2:926-928. 1973.

39. Mays, E.T., W.M. Christopherson, M.M. Mahr, and H.C. Williams, Hepatic Changes in Young Women Ingesting Contraceptive Steroids, Hepatic Hemorrhage and Primary Hepatic Tumors, Journal of the American Medical Association 235:730-782, 1976.

40. Edmondson, H.A., B. Henderson, and B. Benton, Liver Cell Adenomas Associated with the Use of Oral Contraceptives, New England Journal of Medicine 294:470-472, 1976.

41. Pteiter, Rl. and S. Van Den Noort, Estrogen Use and Stroke Risk in Postmenopausal Women, American Journal of Epidemiology 103:445-456, 1976.

ADVANCED PHARMACEUTICAL TECHNOLOGY

132 South Central Avenue, Elmsford, NY 10523

ESTRA-25 PELLETS ESTRA-50 PELLETS Brand of Estradiol N.F. 25MG and 50MG PELLETS PATIENT INFORMATION

WHAT YOU SHOULD KNOW ABOUT ESTROGENS

Estrogens are female hormones produced by the ovaries. The ovaries make several different kinds of

estrogens. In addition, scientists have been able to make a variety of synthetic estrogens. As far as we

know, all these estrogens have similar properties and therefore much the same usefulness, side effects,

and risks. This leaflet is intended to help you understand what estrogens are used for, the risks involved

in their use, and how to use them as safely as possible.

This leaflet includes the most important information about estrogens, but not all the information.

If you want to know more, you can ask your doctor or pharmacist to let you read the package insert

prepared for the doctor.

USES OF ESTROGEN

Estrogens are prescribed by doctors for a number of purposes, including:

1. To provide estrogen during a period of adjustment when a woman's ovaries no longer produce it,

in order to prevent certain uncomfortable symptoms of estrogen deficiency. (All women normally stop

producing estrogens, generally between the ages of 45 and 55: this is called the menopause.)

2. To prevent symptoms of estrogen deficiency when a woman's ovaries have been removed surgically

before the natural menopause.

3. To prevent pregnancy. (Estrogens are given along with a progestagen, another female hormone:

these combinations are called oral contraceptives or birth control pills. Patient labeling is available to

women taking oral contraceptives and they will not be discussed in this leaflet.)

4. To treat certain cancers in woman and men.

5. To prevent painful swelling of the breasts after pregnancy in women who choose not to nurse their babies.

THERE IS NO PROPER USE OF ESTROGEN IN A PREGNANT WOMAN.

ESTROGENS IN THE MENOPAUSE

In the natural course of their lives, all women eventually experience a decrease in estrogen production.

This usually occurs between ages 45 and 55 but may occur earlier or later. Sometimes the ovaries may

need to be removed before natural menopause by an operation, producing a "surgical menopause."

When the amount of estrogen in the blood begins to decrease, many women may develop typical

symptoms: Feelings of warmth in the face, neck and chest or sudden intense episodes of heat and

sweating throughout the body (called "hot flashes" or "hot flushes"). These symptoms are sometimes

very uncomfortable. A few women eventually develop changes in the vagina (called "atrophic vaginitis")

which cause discomfort, especially during and after intercourse.

Estrogens can be prescribed to treat these symptoms of the menopause. It is estimated that

considerably more than half of all women undergoing the menopause have only mild symptoms or

no symptoms at all and therefore do not need estrogens. Other women may need estrogens for a few

months, while their bodies adjust to lower estrogen levels. Sometimes the need will be for periods longer

than six months. In an attempt to avoid over-stimulation of the uterus (womb), estrogens are usually

given cyclically during each month of use, that is three weeks of pills followed by one week without pills.

Sometimes women experience nervous symptoms or depression during menopause. There is no

evidence that estrogens are effective for such symptoms and they should not be used to treat them,

although other treatment may be needed.

You may have heard that taking estrogens for long periods (years) after the menopause will keep your

skin soft and supple and keep you feeling young. There is no evidence that this is so, however, and such

long-term treatment carries important risks.

ESTROGENS TO PREVENT SWELLING OF THE BREASTS AFTER PREGNANCY

If you do not breast feed your baby after delivery, your breasts may fill up with milk and become

painful and engorged. This usually begins about 3 to 4 days after delivery and may last for a few days to

up to a week or more. Sometimes the discomfort is severe, but usually it is not and can be controlled by

pain relieving drugs such as aspirin and by binding the breasts up tightly. Estrogens can be used to try

to prevent the breasts from filling up. While this treatment is sometimes successful, in many cases the

breasts fill up to some degree in spite of treatment. The dose of estrogens needed to prevent pain and

swelling of the breasts is much larger than the dose needed to treat symptoms of the menopause and

this may increase your chances of developing blood clots in the legs or lungs (see below). Therefore,

it is important that you discuss the benefits and the risks of estrogen use with your doctor if you have

decided not to breast feed your baby.

THE DANGERS OF ESTROGENS

1. Cancer of the uterus. If estrogens are used in the postmenopausal period for more than a year,

there is an increased risk of endometrial cancer (cancer of the uterus). Women taking estrogens have

roughly 5 to 10 times as great a chance of getting this cancer as women who take no estrogens. To put

this another way, while a postmenopausal woman not taking estrogens has 1 chance in 1,000 each

year of getting cancer of the uterus, a woman taking estrogens, has 5 to 10 chances in 1,000 each year.

For this reason, it is important to take estrogens only when you really need them.

The risk of this cancer is greater the longer estrogens are used and also seems to be greater when

larger doses are taken. For this reason it is important to take the lowest dose of estrogen that will control

symptoms and to take it only as long as it is needed. If estrogens are needed for longer periods of time,

your doctor will want to reevaluate your need for estrogens at least every six months.

Women using estrogens should report any irregular vaginal bleeding to their doctors; such bleeding

may be of no importance, but it can be an early warning of cancer of the uterus. If you have undiagnosed

vaginal bleeding, you should not use estrogens until a diagnosis is made and you are certain there is

no cancer of the uterus.

If you have had your uterus completely removed (total hysterectomy), there is no danger of developing

cancer of the uterus.

2. Other possible cancers. Estrogens can cause development of other tumors in animals, such as

tumors of the breast, cervix, vagina, or liver, when given for a long time. At present there is no good

evidence that women using estrogen in the menopause have an increased risk of such tumors, but

there is no way yet to be sure they do not: and one study raises the possibility that use of estrogens in

the menopause may increase the risk of breast cancer many years later. This is a further reason to use

estrogens only when clearly needed. While you are taking estrogens, it is important that you go to your

doctor at least once a year for a physical examination. Also, if members of your family have had breast

cancer or if you have breast nodules or abnormal mammograms (breast x-rays), your doctor may wish

to carry out more frequent examinations of your breasts.

3. Gall bladder disease. Women who use estrogens after menopause are more likely to develop gall

bladder disease needing surgery as women who do not use estrogens. Birth control pills have a similar effect.

4. Abnormal blood clotting. Oral contraceptives increase the risk of blood clotting in various parts of

the body. This can result in a stroke (if the clot is in the brain), a heart attack (clot in a blood vessel of

the heart), or a pulmonary embolus (a clot which forms in the leg or pelvis, then breaks off and travels

to the lungs). Any of these can be fatal.

At this time use of estrogens in the menopause is not known to cause such blood clotting, but this has

not been fully studied, and there could still prove to be such a risk. It is recommended that if you have

had clotting in the legs or lungs or a heart attack or stroke while you were using estrogens or birth control

pills, you should not use estrogens (unless they are being used to treat cancer of the breast or prostate). If

you have had a stroke or heart attack or if you have angina pectoris, estrogens should be used with

great caution and only if clearly needed (for example, if you have severe symptoms of the menopause).

The larger doses of estrogen used to prevent swelling of the breasts after pregnancy have been

reported to cause clotting in the legs and lungs.

SPECIAL WARNING ABOUT PREGNANCY

You should not receive estrogen if you are pregnant. If this should occur, there is a greater than usual

chance that the developing child will be born with a birth defect, although the possibility remains fairly small.

A female child may have an increased risk of developing cancer of the vagina or cervix later in life in the

teens or twenties. Every possible effort should be made to avoid exposure to estrogens during pregnancy.

If exposure occurs, see your doctor.

OTHER EFFECTS OF ESTROGENS

In addition to the serious known risks of estrogens described above, estrogens have the following

side effects and potential risks:

1. Nausea and vomiting. The most common side effect of estrogen therapy is nausea. Vomiting is

less common.

2. Effect on breasts. Estrogens may cause breast tenderness or enlargement and may cause the

breasts to secrete a liquid. These effects are not dangerous.

3. Effects on the uterus. Estrogens may cause benign fibroid tumors of the uterus to get larger.

Some women will have menstrual bleeding when estrogens are stopped. But if the bleeding occurs

on days you are still taking estrogens you should report this to your doctor.

4. Effects on liver. Women taking oral contraceptives develop on rare occasions a tumor of the liver

which can rupture and bleed into the abdomen. So far, these tumors have not been reported in women

using estrogens in the menopause, but you should report any swelling or unusual pain or tenderness in

the abdomen to your doctor immediately.

Women with a past history of jaundice (yellowing of the skin and white parts of the eyes) may get

jaundice again during estrogen use. If this occurs, stop taking estrogens and see your doctor.

5. Other effects. Estrogens may cause excess fluid to be retained in the body. This may make some

conditions worse, such as epilepsy, migraine, heart disease, or kidney disease.

SUMMARY

Estrogens have important uses, but they have serious risks as well. You must decide, with your

doctor, whether the risks are acceptable to you in view of the benefits of treatment. Except where your

doctor has prescribed estrogens for use in special cases of cancer of the breast or prostate, you should

not use estrogens if you have cancer of the breast or uterus, are pregnant, have undiagnosed abnormal

vaginal bleeding, clotting in the legs or lungs, or have had a stroke, heart attack or angina, or clotting in

the legs or lungs in the past while you were taking estrogens.

You can use estrogens as safely as possible by understanding that your doctor will require regular

physical examinations while you are taking them and will try to discontinue the drug as soon as possible

and use the smallest dose possible. Be alert for signs of trouble including:

1. Abnormal bleeding from the vagina.

2. Pains in the calves or chest or sudden shortness of breast, or coughing blood (indicating possible

clots in the legs, heart, or lungs).

3. Severe headache, dizziness, faintness, or changes in vision (indicating possible developing clots

in the brain or eye).

4. Breast lumps (you should ask your doctor how to examine your own breasts).

5. Jaundice (yellowing of the skin).

6. Mental depression.

Based on his or her assessment of your medical needs, your doctor has prescribed this drug for you.

Do not give the drug to anyone else.

HOW SUPPLIED

ESTRA-25 & ESTRA-50 are supplied simply in sealed glass ampoules, each pack contains 10 sterile pellets.

ADVANCED PHARMACEUTICAL TECHNOLOGY

132 South Central Avenue, Elmsford, NY 10523